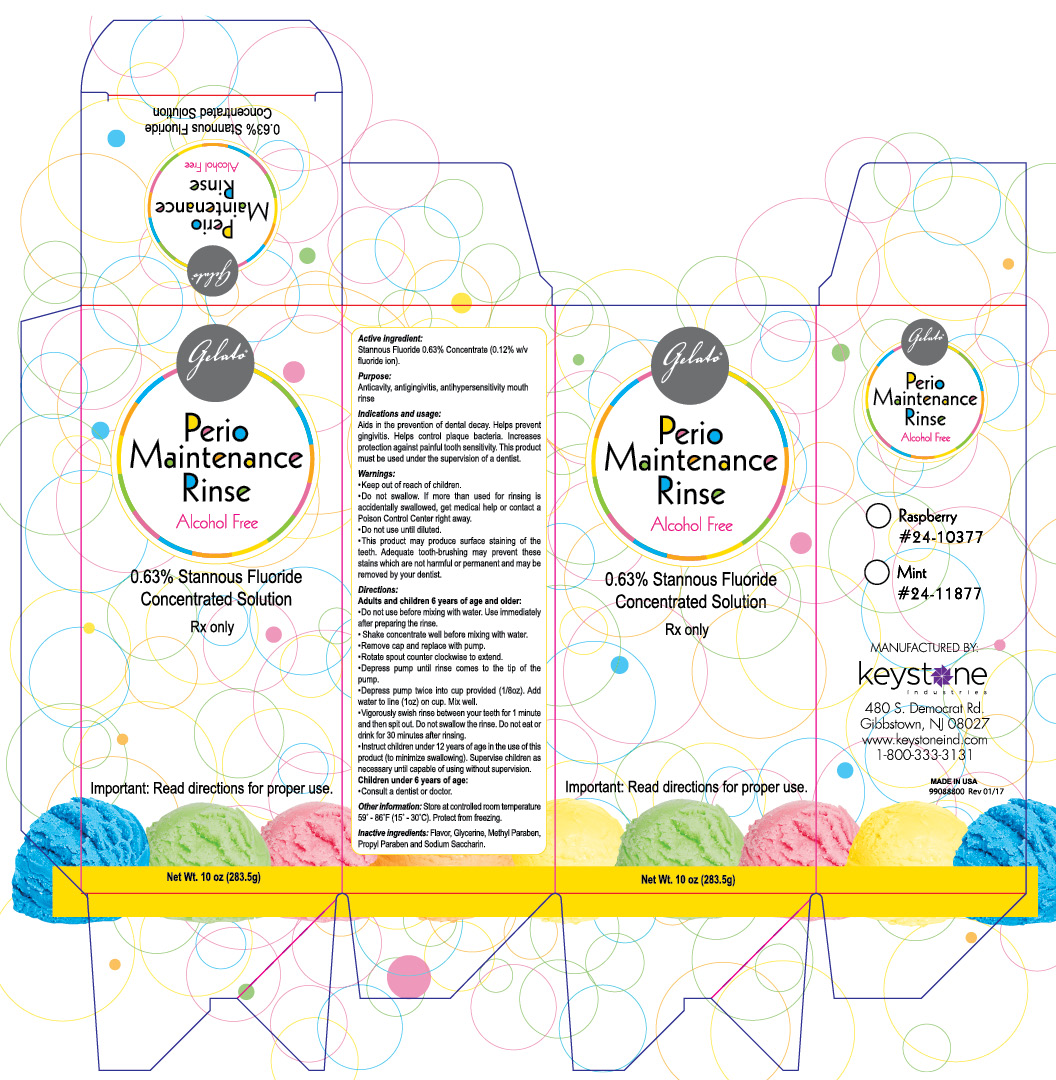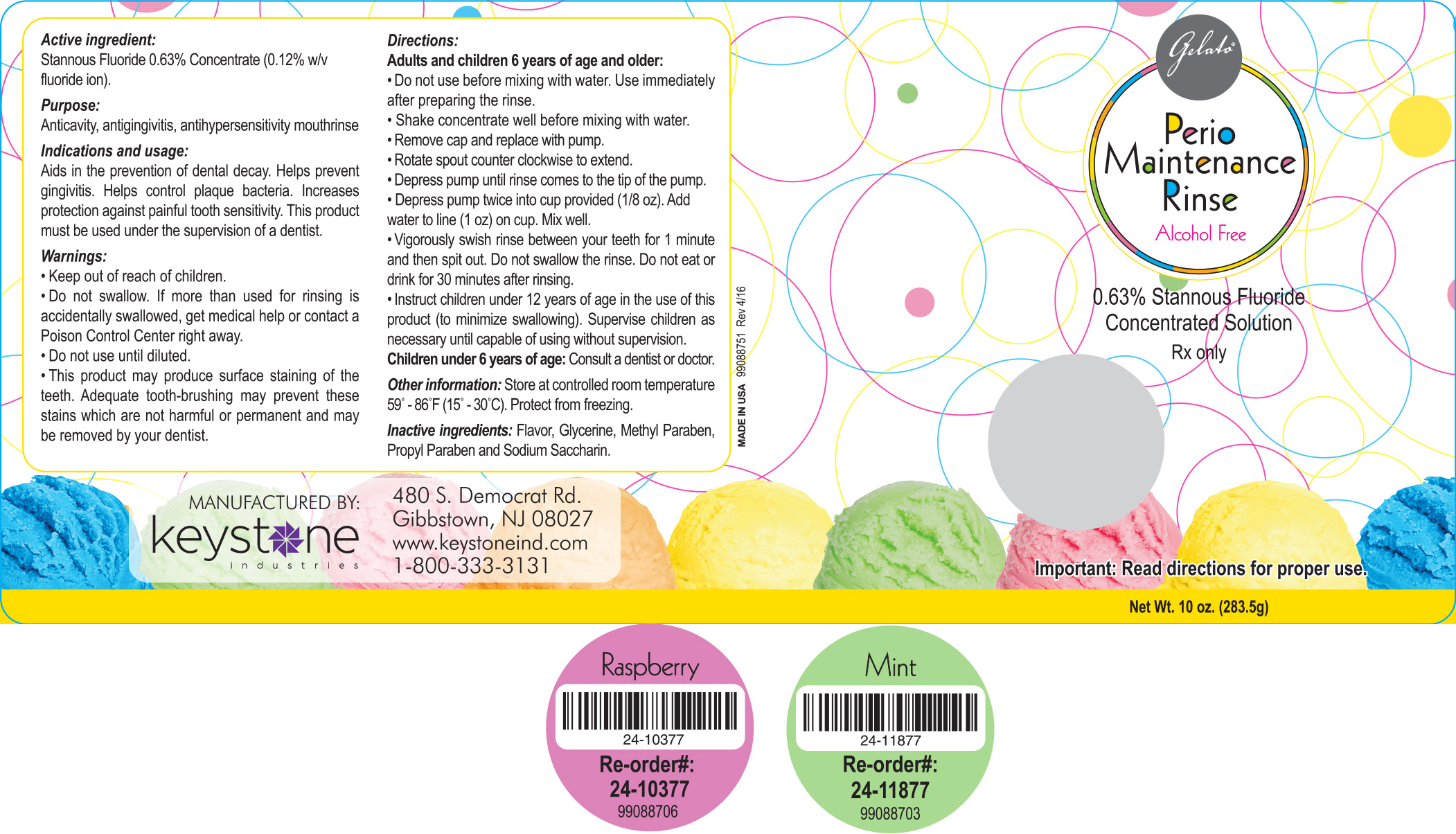 DRUG LABEL: Gelato Perio Maintenance Rinse
NDC: 68400-202 | Form: CONCENTRATE
Manufacturer: Mycone Dental Supply Co., Inc DBA Keystone Industries and Deepak Products Inc.
Category: prescription | Type: HUMAN PRESCRIPTION DRUG LABEL
Date: 20250717

ACTIVE INGREDIENTS: STANNOUS FLUORIDE 0.34 g/283.5 g
INACTIVE INGREDIENTS: GLYCERIN; METHYLPARABEN; PROPYLPARABEN; SACCHARIN SODIUM

Active Ingredient:

Stannous Fluoride 0.63% Concentrate (0.12% w/v fluoride ion).

Purpose:

Anticavity, antigingivitis, antihypersensitivity mouthrinse

Indications and Usage:

Aids in the prevention of dental decay. Helps prevent gingivitis. Helps control plaque bacteria. Increases protection against painful tooth sensitivity. This product mist be used under the supervision of a dentist.

Warnings:

- Keep out of reach of children.
- Do not swallow. If more than used for rinsing is accidentally swallowed, get medical help or contact a Poison Control Center right away.
- Do not use until diluted.
- This product may produce surface staining of the teeth.
- This product may produce surface staining of the teeth. Adequate tooth-brushing may prevent these stains which are not harmful or permanent and may be removed by your dentist.

Directions:

Adults and children 6 years of age and older:

- Do not use before mixing with water. Use immediately after preparing the rinse.
- Shake concentrate well before mixing with water.
- Remove cap and replace with pump.
- Rotate spout counter clockwise to extend.
- Depress pump until rinse comes to the tip of the pump.
- Depress pump twice into cup provided (1/8oz). Add water to line (1oz) on cup. Mix well.
- Vigorously swish rinse between your teeth for 1 minute and then spit out. Do not swallow the rinse. Do not eat or drink for 30 minutes after rinsing.
- Instruct children under 12 years of age in the use of this product (to minimize swallowing). Supervise children as necessary until capable of using without supervision.

Children under 6 years of age: Consult a dentist or doctor.

Inactive Ingredients:

Flavor, Glycerin, Methyl Paraben, Propyl Paraben and Sodium Saccharin.

Other Information:

Store at controlled room temperature 59° - 86°F (15°-30°C). Protect from freezing.